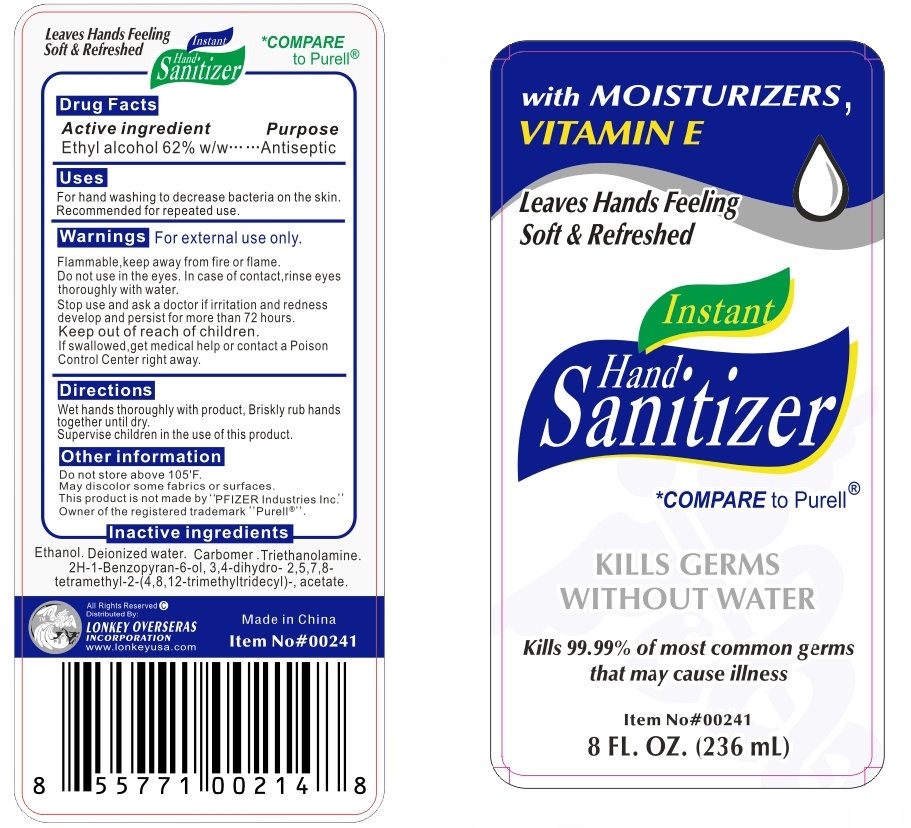 DRUG LABEL: Instant Hand Sanitizer
NDC: 42302-030 | Form: LIQUID
Manufacturer: Lonkey Overseas Inc.
Category: otc | Type: HUMAN OTC DRUG LABEL
Date: 20120125

ACTIVE INGREDIENTS: ALCOHOL 62 mL/100 mL
INACTIVE INGREDIENTS: ALCOHOL; WATER; TROLAMINE; .ALPHA.-TOCOPHEROL ACETATE, D-

Instant Hand Sanitizer

Active Ingredient:

Ethyl Alcohol 62% w/w

Purpose

Antiseptic

Uses:

For handwashing to decrease bacteria on the skin.

Recommended for repeated use.

Warnings

For external use only.

OTHER SAFETY INFORMATION

Flammable, keep away from fire or flame.

Do not use in the eyes. In case of contact, rinse eyes thoroughly with water.

Stop use and ask a doctor if irritation and redness develop and persist for more than 72 hours.

Keep out of reach of children.

If swallowed, get medical help or contact a Poison Control Center right away.

Directions

Wet hands thoroughly with product. Briskly rub hands together until dry.

Supervise children in the use of this product.

Inactive Ingredients

Ethanol, Deionized water, Carbomer, Triethanolamine, 2H-1-Benzopyran-6-ol,3,4-dihydro-2,5,7,8-tetramethyl-2-(4,8,12-trimethyltridecyl)-acetate.

Other Information

Do not store above 105 degrees F.

May discolor some fabrics or surfaces.

This product is not made by "PFIZER Industries Inc."

Owner of the registered trademark "Purell"

All Rights Reserved

Distributed By:

LONKEY OVERSEAS INCORPORATION

MADE IN CHINA

Instant Hand Sanitizer 8oz/236ml (42302-030-00)

with MOISTURIZERS,
VITAMIN E
Leaves Hands Feeling
Soft and Refreshed
Instant
Hand Sanitizer
COMPARE to Purell
KILLS GERMS
WITHOUT WATER
Kills 99.99% of most common germs
that may cause illness
Item No 00241
8 FL. OZ (236 ml)